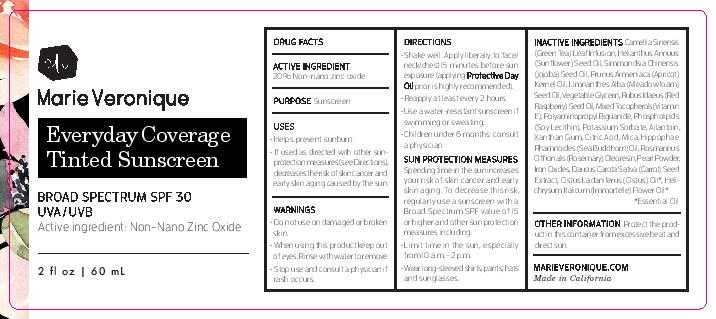 DRUG LABEL: Everyday Coverage Tinted Sunscreen - Extra Light Tint
NDC: 72592-001 | Form: CREAM
Manufacturer: MV Advanced
Category: otc | Type: HUMAN OTC DRUG LABEL
Date: 20241212

ACTIVE INGREDIENTS: ZINC OXIDE 200 mg/1 mL
INACTIVE INGREDIENTS: GREEN TEA LEAF; APRICOT KERNEL OIL; MEADOWFOAM SEED OIL; SUNFLOWER OIL; GLYCERIN; RASPBERRY SEED OIL; TOCOPHEROL; LECITHIN, SOYBEAN; HIPPOPHAE RHAMNOIDES SEED OIL; LABDANUM OIL; JOJOBA OIL; MICA; POTASSIUM SORBATE; ALLANTOIN; XANTHAN GUM; ROSEMARY OIL; CITRIC ACID MONOHYDRATE; BIGUANIDE; PEARL (HYRIOPSIS CUMINGII); FERROUS OXIDE; DAUCUS CAROTA SUBSP. SATIVUS SEED; HELICHRYSUM ITALICUM FLOWER OIL

Drug Facts

ACTIVE INGREDIENT:

20% non-nano zinc oxide

PURPOSE

Sunscreen

INDICATIONS AND USAGE

- Helps prevent sunburn
- If used as directed with other sun-protection measures (see Directions), decreases the risk of skin cancer and early skin aging caused by the sun.

INACTIVE INGREDIENT

Camellia Sinensis (Green Tea) Leaf Infusion, Helianthus Annuus (Sunflower) Seed Oil, Simmondsia Chinensis (Jojoba) Seed Oil, Prunus Armeniaca (Apricot) Kernel Oil, Limnanthes Alba (Meadowfoam) Seed Oil, Vegetable Glycerin, Rubus Idaeus (Red Raspberry) Seed Oil, Mixed Tocopherols (Vitamin E), Polyaminopropyl Biguanide, Phospholipids (Soy Lecithin), Potassium Sorbate, Allantoin, Xanthan Gum, Citric Acid, Mica, Hippophae Rhamnoides (Sea Buckthorn) Oil, Rosmarinus Officinalis (Rosemary) Oleoresin, Pearl Powder, Iron Oxides, Daucus Carota Sativa (Carrot) Seed Extract, Cistus Ladaniferus (Cistus) Oil*, Helichrysum Italicum (Immortelle) Flower Oil*

*Essential Oil

- Do not use on damaged or broken skin.
- When using this product keep out of eyes. Rinse with water to remove.
- Stop use and consult a physician if rash occurs.

DOSAGE AND ADMINISTRATION

- Shake well. Apply liberally to face/neck/chest 15 minutes before sun exposure (applying Protective Day Oilprior is highly recommended).
- Reapply at least every 2 hours.
- Use a water-resistant sunscreen if swimming or sweating.
- Children under 6 months: consult a physician.

Sun Protection Measures

Spending time in the sun increases your risk of skin cancer and early skin aging. To decrease this risk, regularly use a sunscreen with a Broad Spectrum SPF value of 15 or higher and other sun protection measures including:

- Limit time in the sun, especially from 10 a.m. - 2 p.m.
- Wear long-sleeved shirts, pants, hats, and sunglasses.

STORAGE AND HANDLING

Protect the product in this container from excessive heat and direct sun.

DESCRIPTION

marieveronique.com

Made in California

PACKAGE LABEL

Marie Veronique

Everyday Coverage Tinted Sunscreen

Broad Spectrum SPF 30 UVA/UVB

Active Ingredient: Non-Nano Zinc Oxide

2 fl oz 60 mL